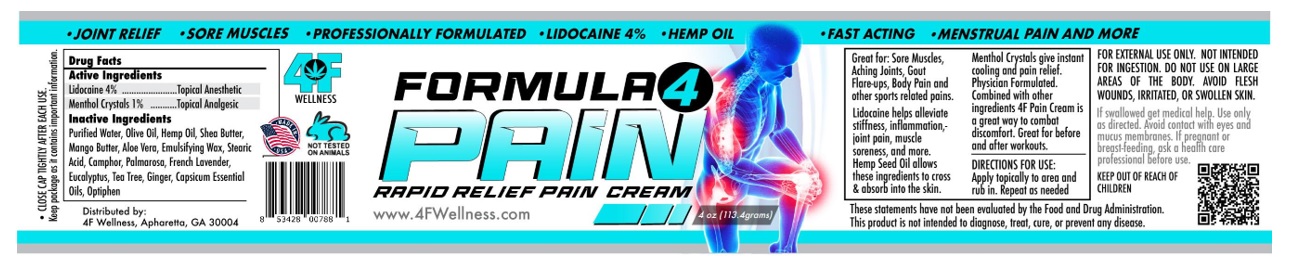 DRUG LABEL: FORMULA 4 PAIN
NDC: 58292-005 | Form: CREAM
Manufacturer: Lifequest Creations LLC
Category: otc | Type: HUMAN OTC DRUG LABEL
Date: 20230703

ACTIVE INGREDIENTS: LIDOCAINE HYDROCHLORIDE 4 g/100 g; MENTHOL, UNSPECIFIED FORM 1 g/100 g
INACTIVE INGREDIENTS: WATER; OLIVE OIL; SHEA BUTTER; MANGO; CANNABIS SATIVA SEED OIL; .ALPHA.-TOCOPHEROL; CETOSTEARYL ALCOHOL; PALMAROSA OIL; TEA TREE OIL; EUCALYPTUS OIL; CAMPHOR (NATURAL); LAVENDER OIL; GINGER OIL; CAPSICUM OLEORESIN; ALOE VERA LEAF; PHENOXYETHANOL; ARNICA MONTANA WHOLE

Active Ingredients Purpose

Lidocaine HCl 4% Topical Anesthetic

Menthol 1% Topical Analgesic

Uses

Fast Pain Relief

Warnings

FOR EXTERNAL USE ONLY. NOT INTENDED FOR INGESTION DONT USE ONLARGE AREAS OF THE BODY OR ON CUT, IRRITATED OR SWOLLEN SKIN. Use only as directed, avoid contact with eyes and mucus membranes If pregnant or breast-feeding, ask a health care professional before use. If swallowed, get medical help

Direction

Apply topically to area.

Inactive ingredients

Purified water, Arnica, EMU OIL, MCT OIL, Hemp seed oil, Glyceryl stearate, Cetearyl Alcohol, Copaiba, Tea Tree, Basil, Rosemary, Rose, Lavender, Ginger, Capsicum, Bergamot

Other information

Great for : Sore muscles, aching joints, gout flare-ups and body pain and other sports related pain.

Menthol crystals gives instant cooling and pain releif. Physician formulated (roll-on-blend) glides on is non-sticky, and absorbs quickly.

Arnica reduces bruising and swelling. Lidocaine helps alleviate stiffness, inflammation, joint pain, muscle soreness and more. Hemp seed oil

allows ingredients to cross and absorb into the skin. With its healing properties, Emu oil reduces fibrosis from skin damage caused by radiation

therapy.